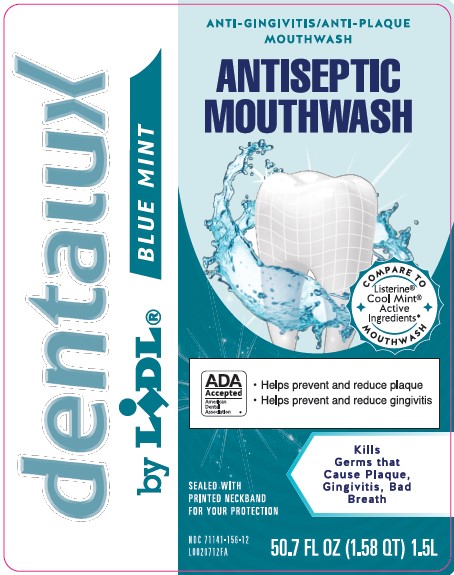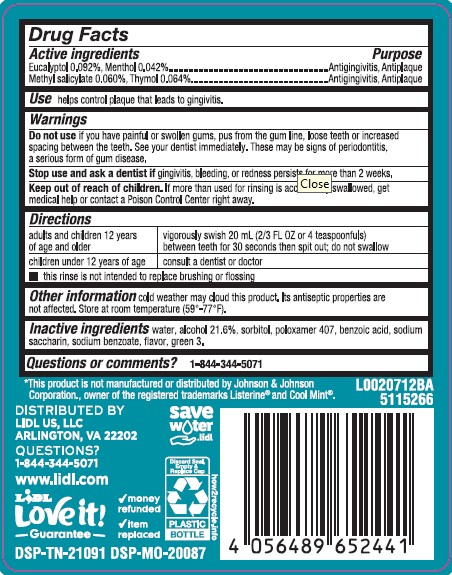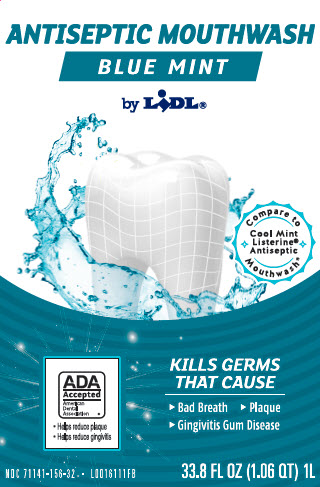 DRUG LABEL: Antispetic
NDC: 71141-156 | Form: MOUTHWASH
Manufacturer: Lidl US, LLC
Category: otc | Type: HUMAN OTC DRUG LABEL
Date: 20260204

ACTIVE INGREDIENTS: EUCALYPTOL 0.92 mg/1 mL; MENTHOL 0.42 mg/1 mL; METHYL SALICYLATE 0.6 mg/1 mL; THYMOL 0.64 mg/1 mL
INACTIVE INGREDIENTS: WATER; ALCOHOL; SORBITOL; POLOXAMER 407; BENZOIC ACID; SACCHARIN SODIUM; SODIUM BENZOATE; FD&C GREEN NO. 3

Dentalux_Lidl 664.003/664AT rev 2 664AU
Blue Mint Antiseptic Mouthrinse

Active ingredients

Eucalyptol 0.092%

Menthol 0.042%

Methyl salicylate 0.060%

Thymol 0.064%

Purpose

Antigingivitis, Antiplaque

Use

helps control plaque that leads to gingivitis

Warnings

for this product

Do not use

if you have painful or swollen gums, pus from the gum line, loose teeth or increased spacing between the teeth. See your dentist immediately. These may be signs of periodontitis, a serious form of gum disease.

Stop use and ask a dentist if

gingivitis, bleeding, or redness persists for more than 2 weeks.

Keep out of reach of children.

If more than used for rinsing is accidentally swallowed, get medical help or contact a Poison Control Center right away.

Directions

adults and children 12 years of age and older - vigorously swish 20 mL (2/3 FL OZ or 4 teaspoonfuls) between teeth for 30 seconds then spit out; do not swallow

children under 12 years of age - consult a dentist or doctor

- this rinse is not intended to replace brushing or flossing

Other information

cold weather may cloud this product. Its antiseptic properties are not affected. Store at room temperature (59°-77°F).

Inactive ingredients

water, alcohol 21.6%, sorbitol, poloxamer 407, benzoic acid, sodium saccharin, sodium benzoate, flavor, green 3

Questions or comments?

1-844-344-5071

*This product is not manufactured or distributed by Johnson & Johnson Corporation., owner of the registered trademarks Listerine® and Cool Mint®.

DISTRIBUTED BY

Lidl US, LLC

Arlington, VA

QUESTIONS

1-844-344-5071

www.Lidl.com

LIDL

Love it! Guarentee

money refunded

item replaced

DSP-TN-21091 DSP-MO-20087

savewater.lidl

Discard Seal, Empty & Replace Cap

Plastic Bottle

how2recycle.info

principal display panel

ANTISEPTIC MOUTHRINSE

BLUE MINT

by LIDL

ADA

ACCEPTED

American

Dental

Association

- Helps reduce plaque
- Helps reduce gingivitis

Kills Germs That Cause Bad Breath, Plaque, Gingivitis

NDC 71141-156-32

33.8 FL OZ (1.06 QT) 1L

principal display panel

dentaux

by LIDL BLUE MINT

ANTI-GINGIVITIS/ANTI-PLAQUE

MOUTHWASH

ADA

ACCEPTED

American

Dental

Association

- Helps reduce plaque
- Helps reduce gingivitis

SEALED WITH PRINTED NECKBAND FOR YOUR PROTECTION

Kills Germs That Cause Plaque, Gingivitis, Bad Breath

NDC 71141-156-12

50.7 FL OZ (1.58 QT) 1.5L